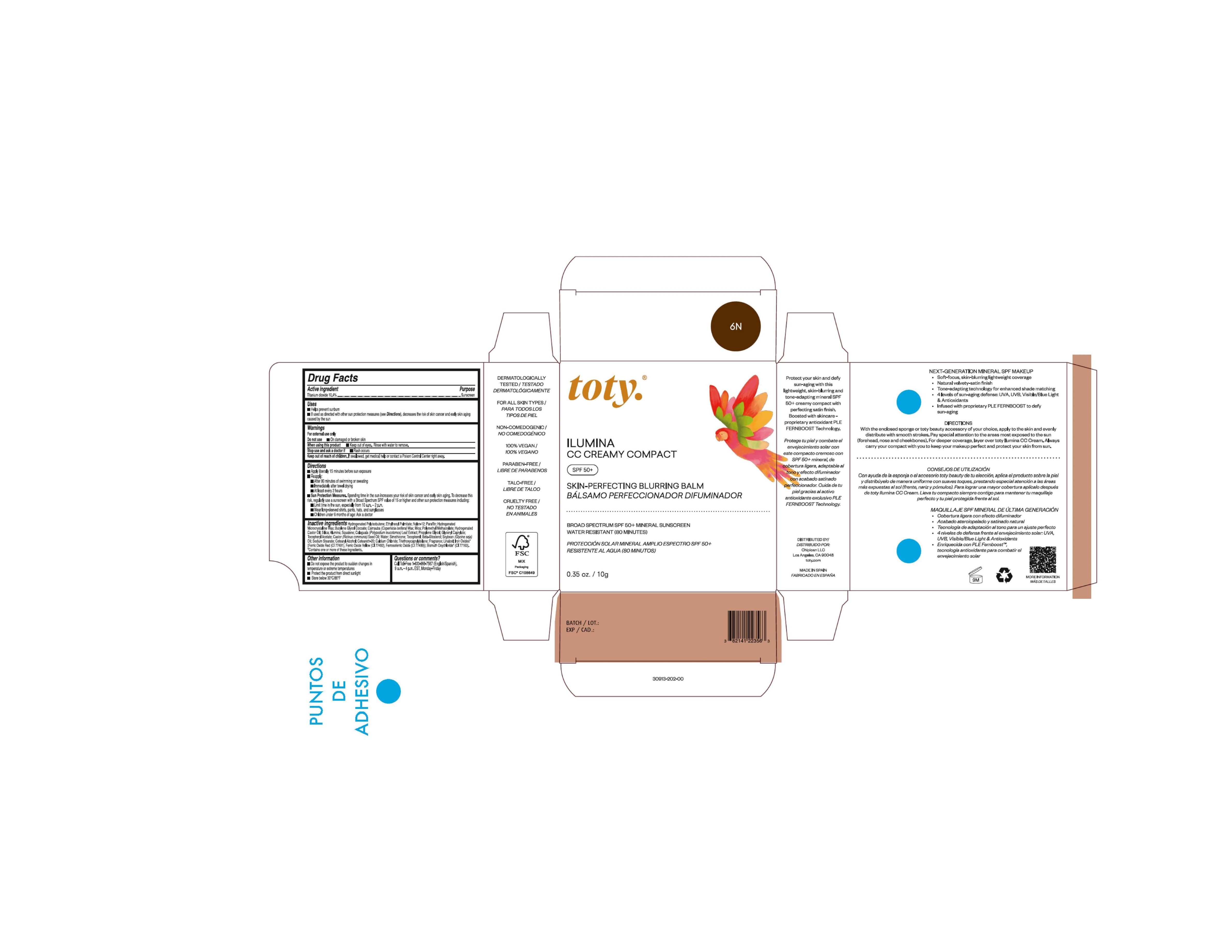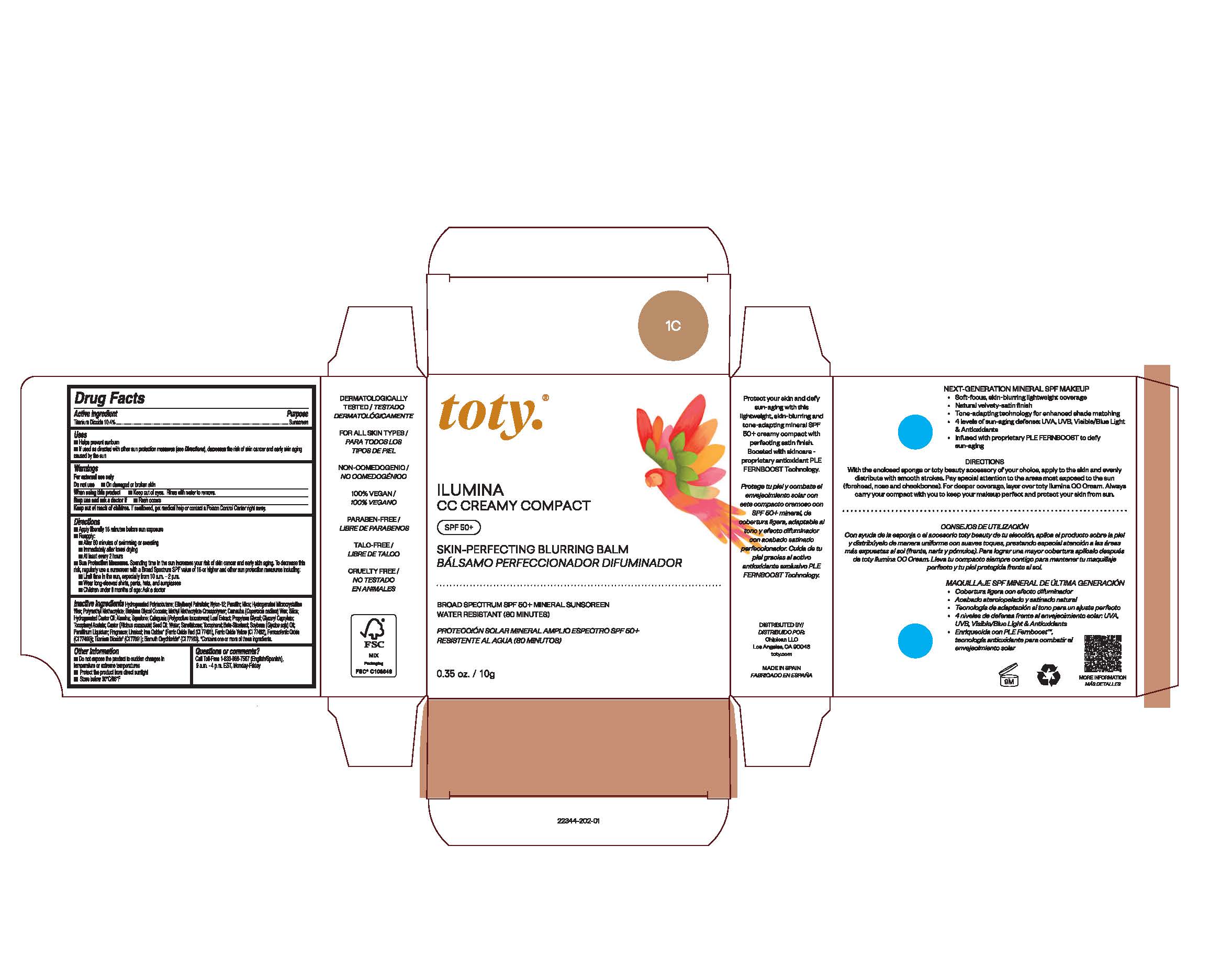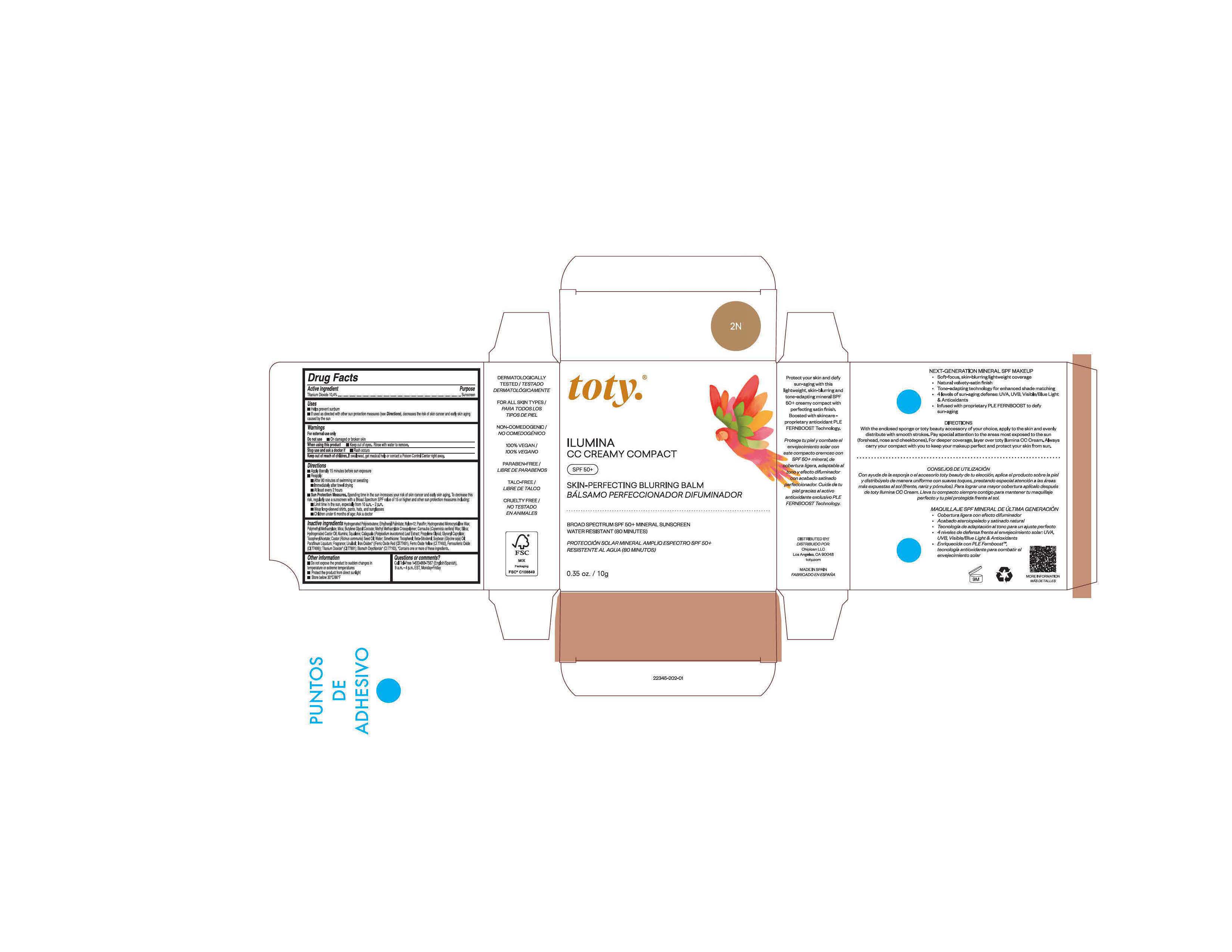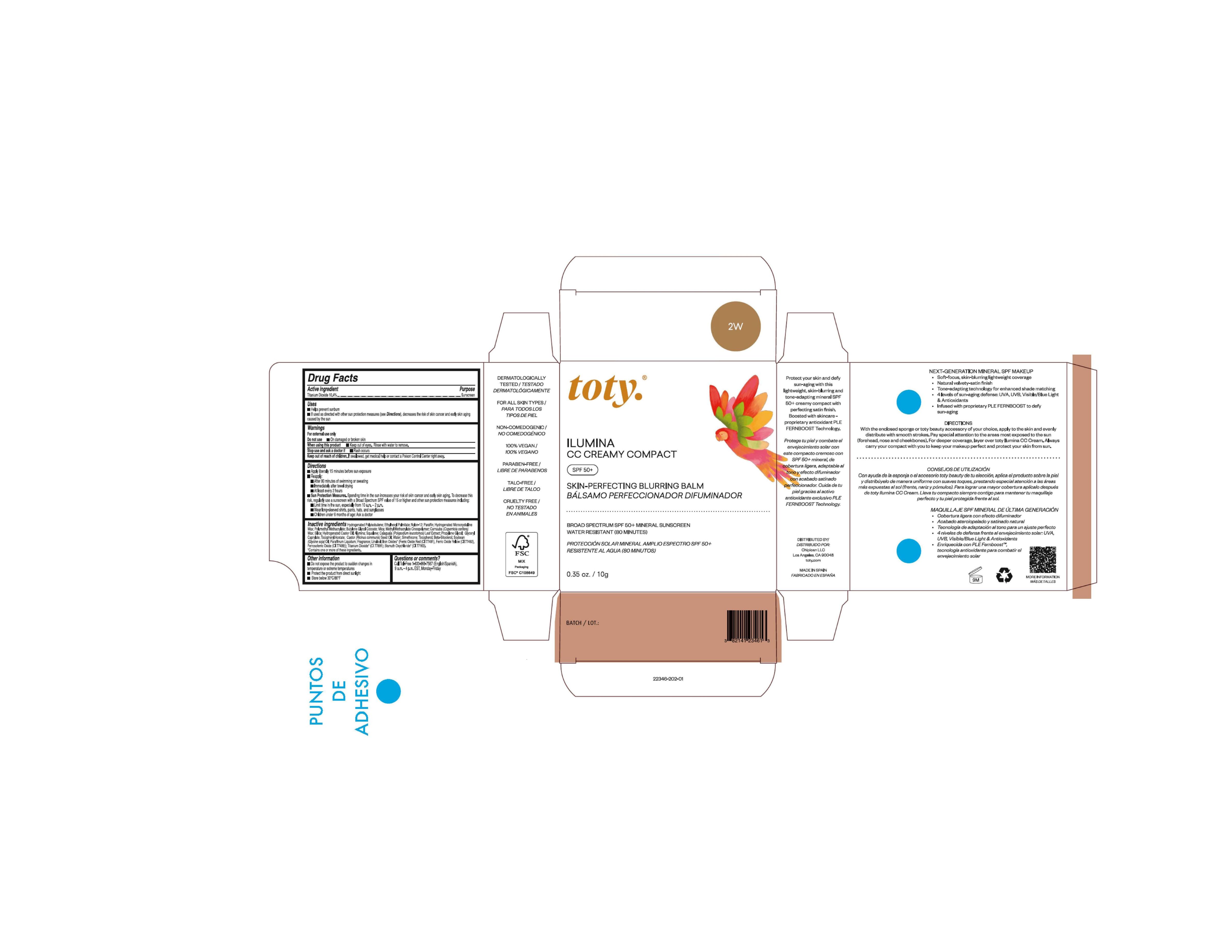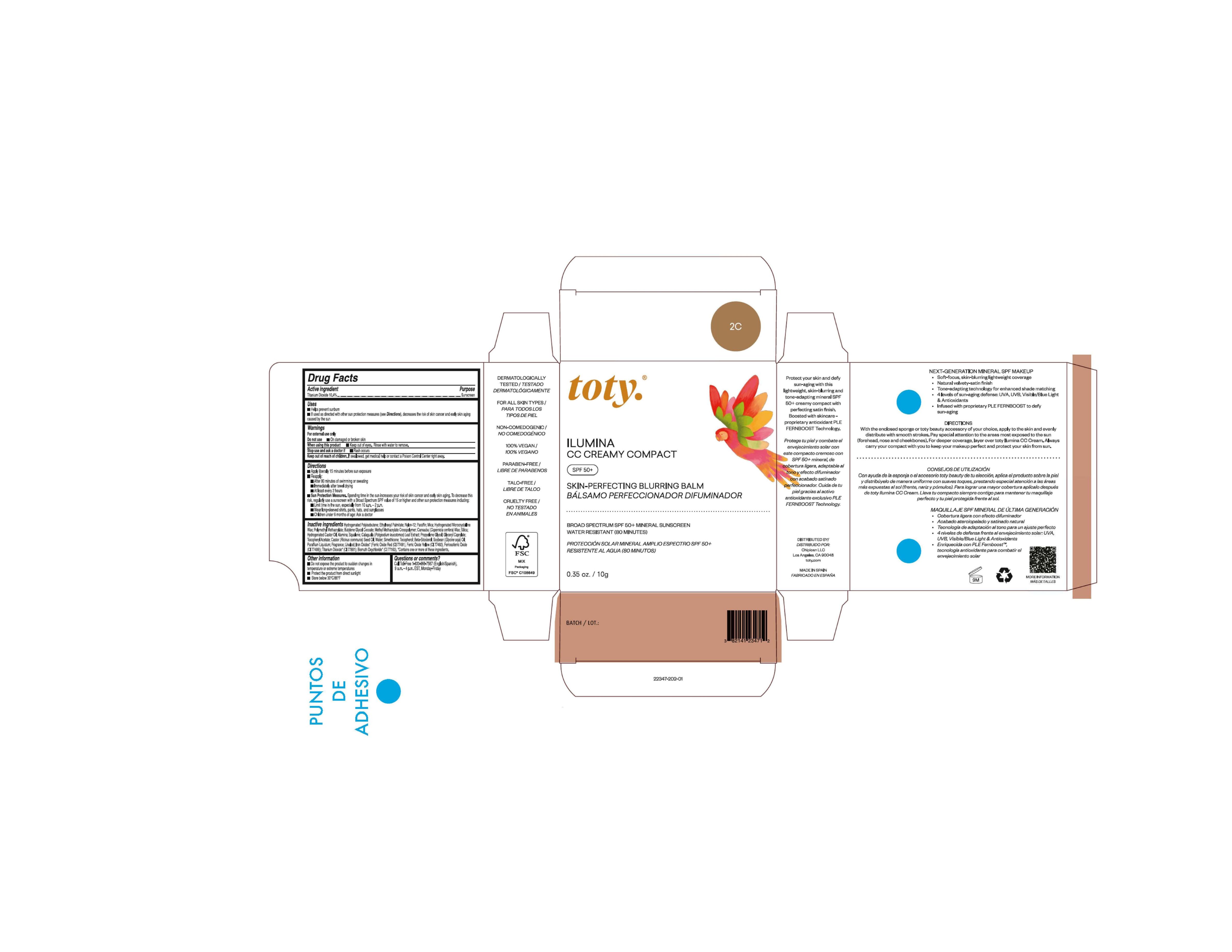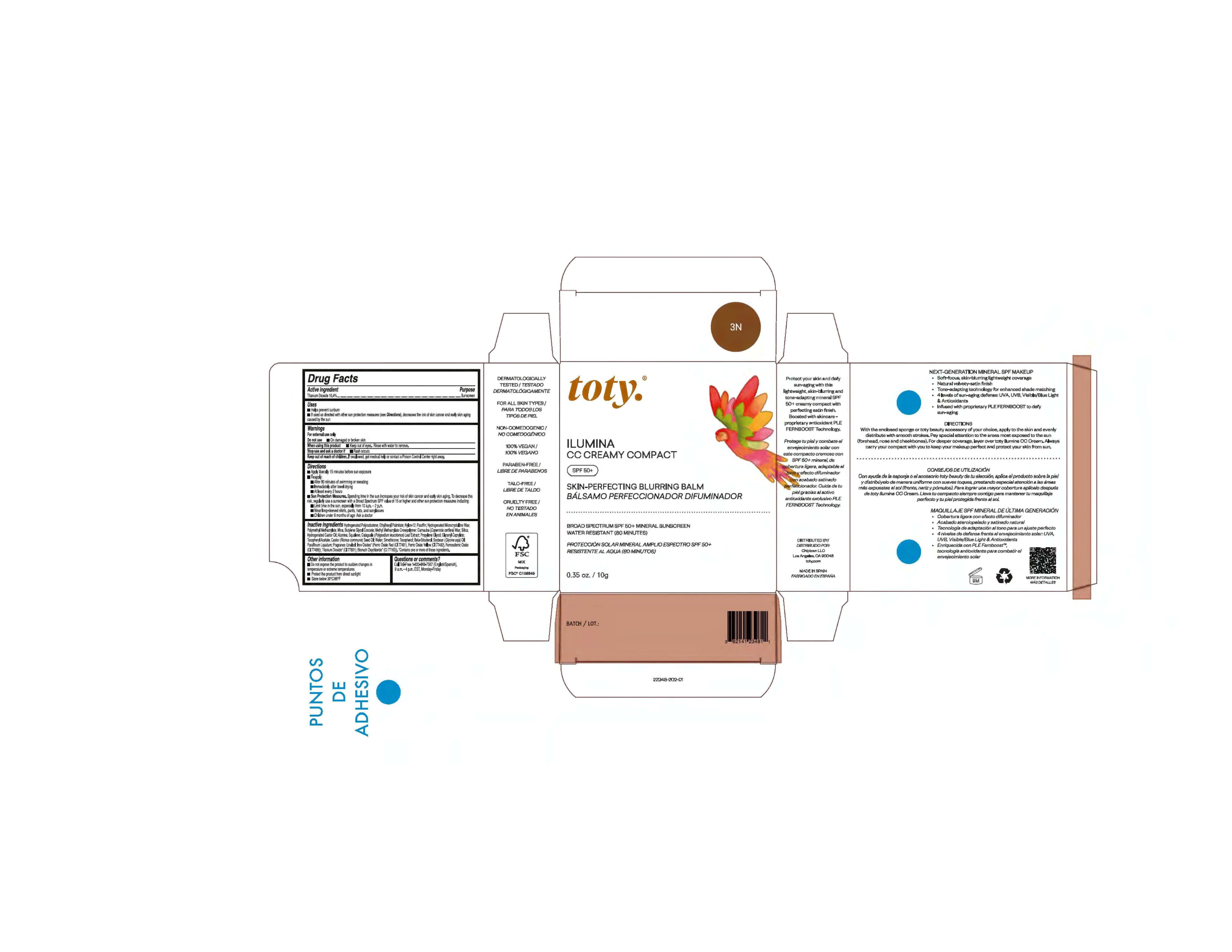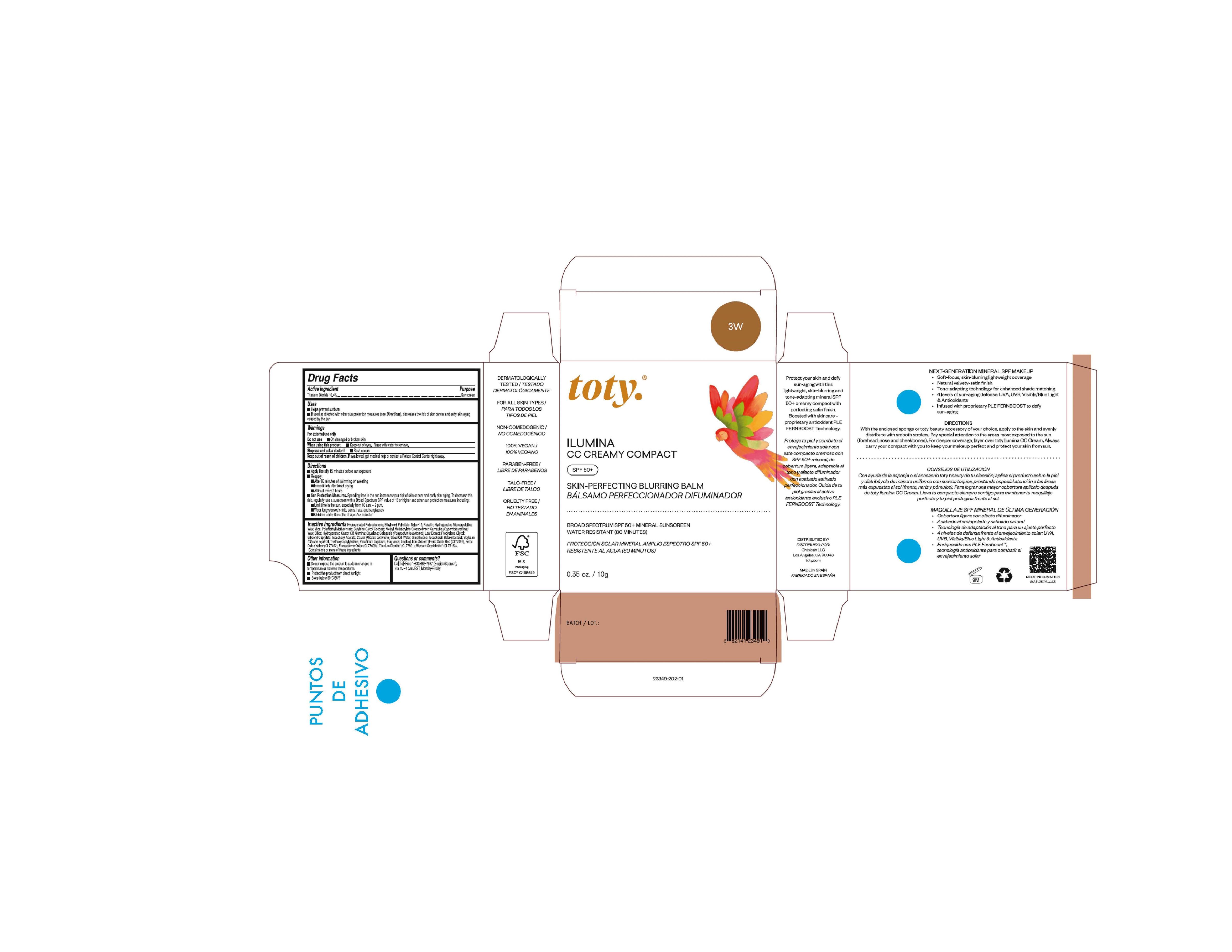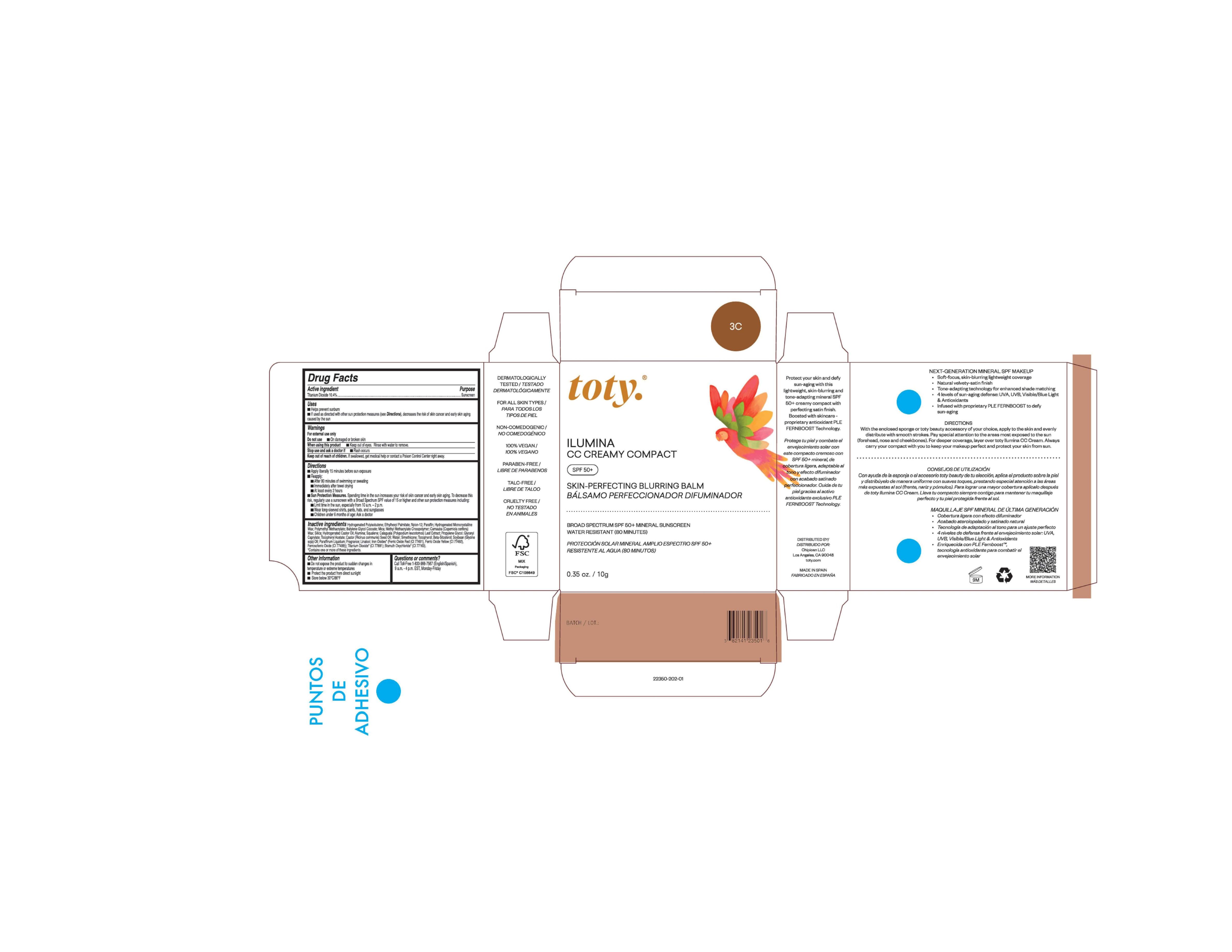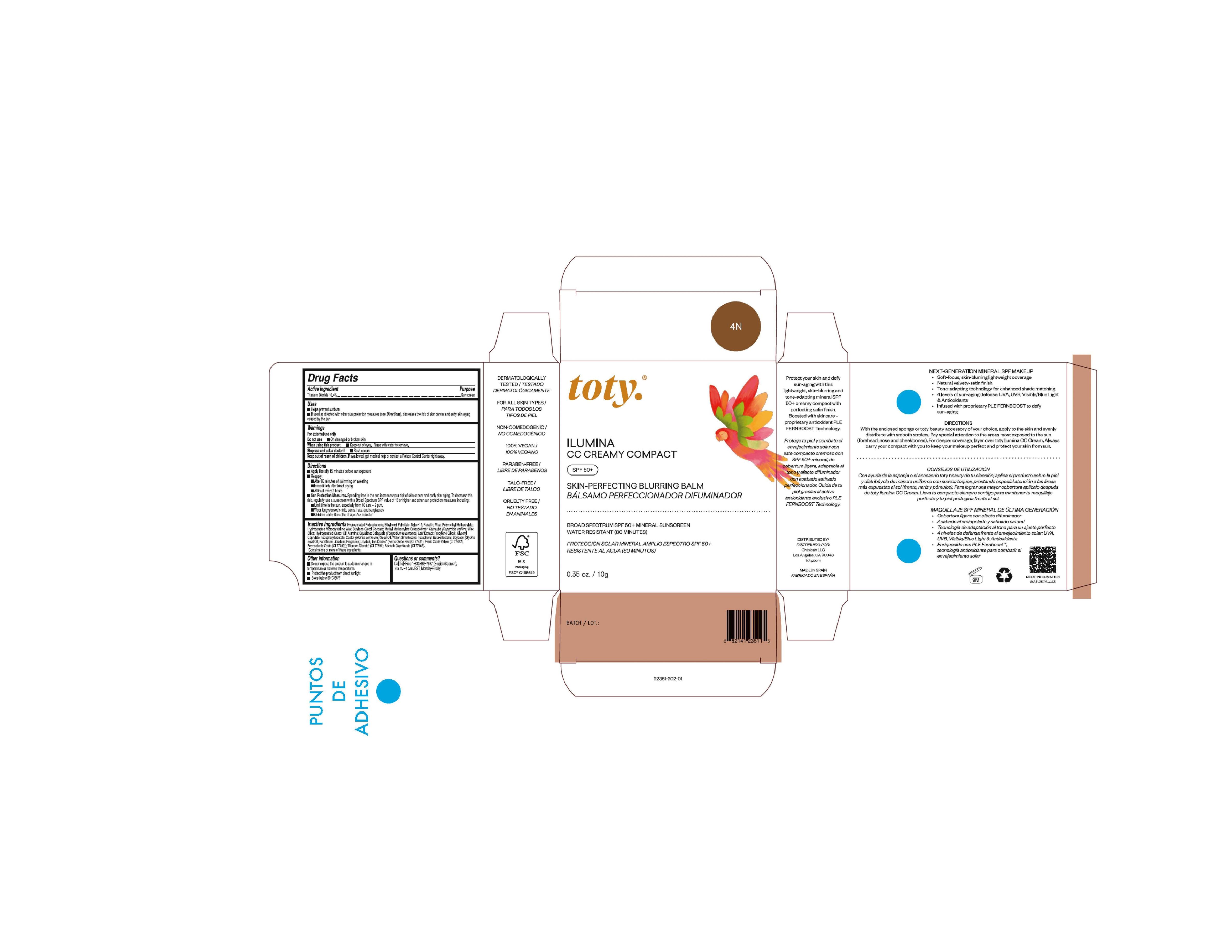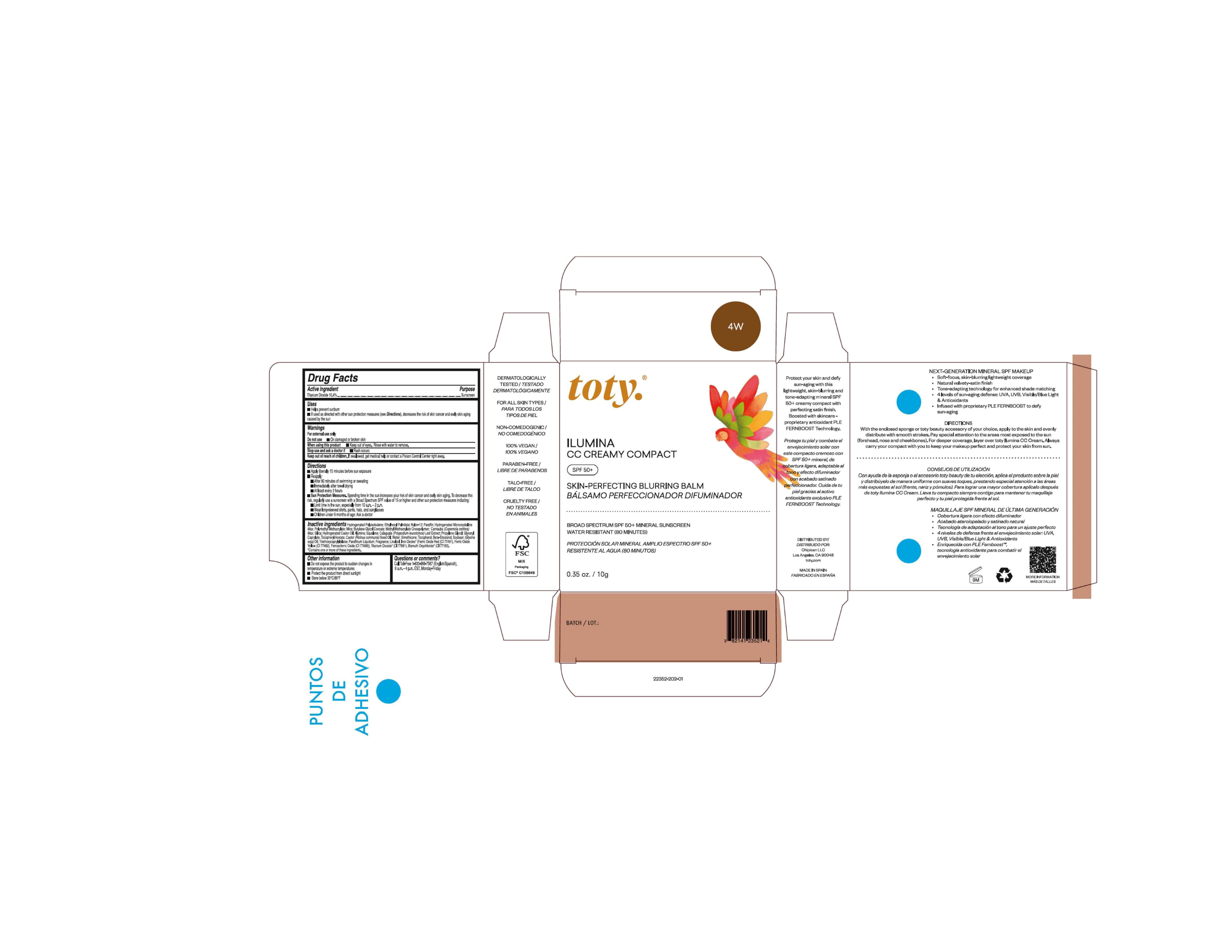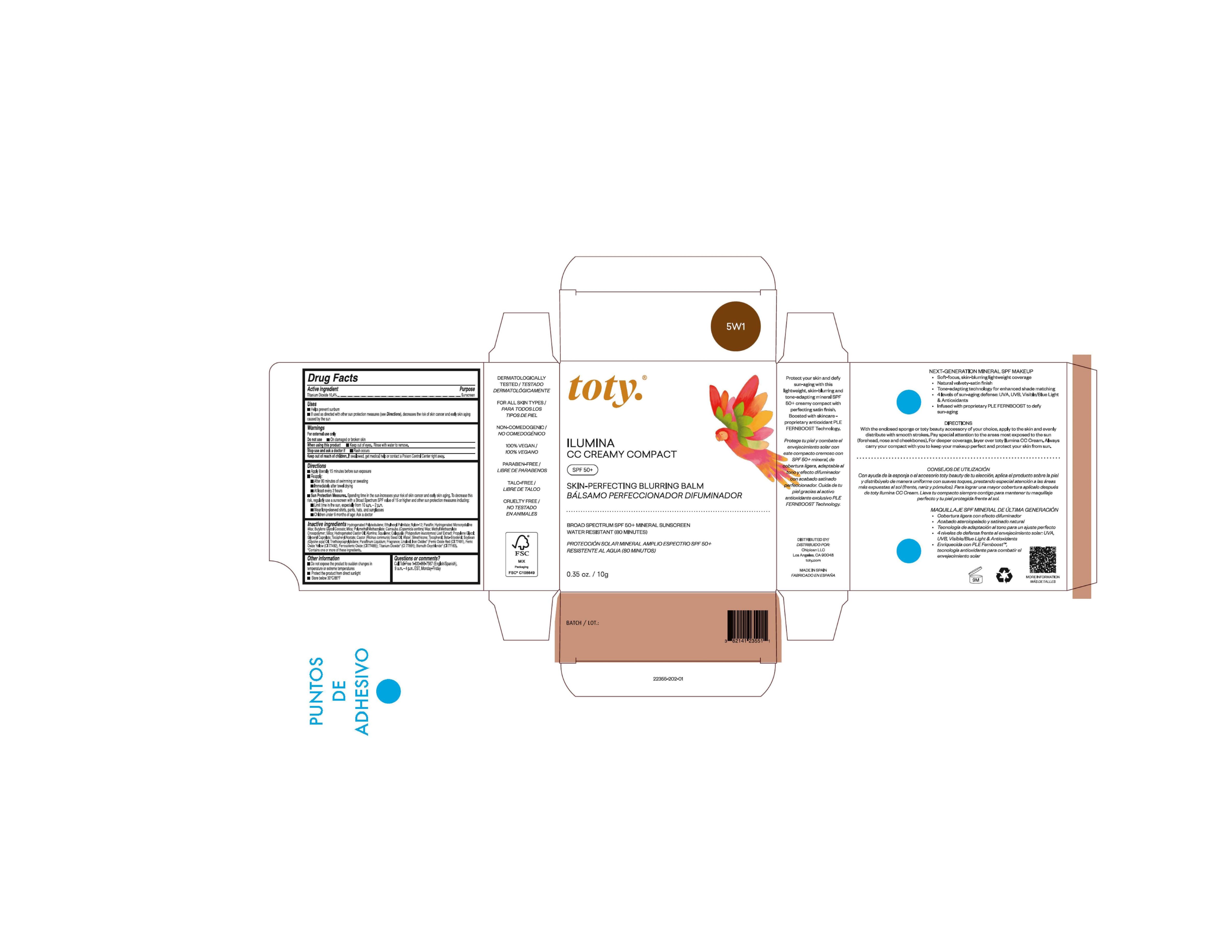 DRUG LABEL: toty Ilumina CC Creamy Compact 2W
NDC: 82141-2346 | Form: CREAM
Manufacturer: Chipican LLC
Category: otc | Type: HUMAN OTC DRUG LABEL
Date: 20250901

ACTIVE INGREDIENTS: TITANIUM DIOXIDE 10.4 g/100 g
INACTIVE INGREDIENTS: FERROSOFERRIC OXIDE; ALUMINUM OXIDE; PARAFFIN; ETHYLHEXYL PALMITATE; MICROCRYSTALLINE WAX; METHYL METHACRYLATE/GLYCOL DIMETHACRYLATE CROSSPOLYMER; POLY(METHYL METHACRYLATE; 450000 MW); PHLEBODIUM AUREUM LEAF; FERRIC OXIDE RED; SILICON DIOXIDE; FERRIC OXIDE YELLOW; MINERAL OIL; 1,2-BUTYLENE GLYCOL MONOCOCOATE; PROPYLENE GLYCOL; SOYBEAN OIL; HYDROGENATED CASTOR OIL; WATER; GLYCERYL CAPRYLATE; .ALPHA.-TOCOPHEROL ACETATE; TOCOPHEROL; NYLON-12; HYDROGENATED POLYBUTENE (1300 MW); MICA; SQUALENE; CASTOR OIL; .BETA.-SITOSTEROL; LINALOOL, (+/-)-; CARNAUBA WAX

toty Ilumina CC Creamy Compact (Godet, Chipican LLC)

Active Ingredient

Titanium Dioxide- 10.4%

Purpose

Sunscreen

Uses

- Helps prevent sunburn

- If used as directed with other sun protection measures (see Directions), decreases the risk of skin cancer and early skin aging caused by the sun

Warnings

For external use only

Do not use On damaged or broken skin

When using this product Keep out of eyes. Rinse with water to remove.

Stop use and ask a doctor if Rash occurs

Keep out of reach of children. If swallowed, get medical help or contact a Poison Control Center right away.

DOSAGE AND ADMINISTRATION

- Apply liberally 15 minutes behore sun exposure
- Reapply:

After 80 minutes of swimming or sweating

Immediately after towel drying

At least every 2 hours

- Sun Protection Measures. Spending time in the sun increases your risk of skin cancer and early skin aging. To decrease this risk, regularly use a sunscreen with a Broad Spectrum SPF value of 15 or higher and other sun protection measures including:

Limit time in the sun, especially from 10 a.m. - 2 p.m.

Wear long-sleeved shirts, pants, hats, and sunglasses

Children under 6 months of age: Ask a doctor.

Other Information

- Do not expose the sudden changes in temperature or extreme temperatures

- Protect the product from direct sunlight

- Store below 30°C/86°F

Inactive Ingredients

NDCs 82141-2344-1 & 82141-2347-1

Hydrogenated Polyisobutene; Ethylhexyl Palmitate; Nylon-12; Paraffin; Mica, Hydrogenated Microcrystalline Wax; Polymethyl Methacrylate; Butylene Glycol Cocoate; Methyl Methacrylate Crosspolymer; Carnauba (Copernica cerifera) Wax; Silica; Hydrogenated Castor Oil; Alumina, Squalene, Calaguala (Polypodium leucotomos) Leaf Extract; Propylene Glycol; Glyceryl Caprylate; Tocopheryl Acetate; Castor (Ricinus communis) Seed Oil; Water; Simethicone; Tocopherol; Beta-Sitosterol; Soybean (Glycine soja) Oil; Paraffinum Liquidum; Fragrance, Linalool, Iron Oxides* (Ferric Oxide Red (CI 77491), Ferric Oxide Yellow (CI 77492), Ferrosoferric Oxide (CI 77499)); Titanium Dioxide* (CI 77891), Bismuth Oxychloride* (CI 77163). * Contains one or more of these ingredients.

NDCs 82141-2345-1 & 82141-2348-1

Hydrogenated Polyisobutene; Ethylhexyl Palmitate; Nylon-12; Paraffin; Hydrogenated Microcrystalline Wax; Polymethyl Methacrylate; Mica; Butylene Glycol Cocoate; Methyl Methacrylate Crosspolymer; Carnauba (Copernica cerifera) Wax; Silica; Hydrogenated Castor Oil; Alumina, Squalene, Calaguala (Polypodium leucotomos) Leaf Extract; Propylene Glycol; Glyceryl Caprylate; Tocopheryl Acetate; Castor (Ricinus communis) Seed Oil; Water; Simethicone; Tocopherol; Beta-Sitosterol; Soybean (Glycine soja) Oil; Paraffinum Liquidum; Fragrance, Linalool, Iron Oxides* (Ferric Oxide Red (CI 77491), Ferric Oxide Yellow (CI 77492), Ferrosoferric Oxide (CI 77499)); Titanium Dioxide* (CI 77891), Bismuth Oxychloride* (CI 77163). * Contains one or more of these ingredients.

NDCs 82141-2346-1 & 82141-2350-1

Hydrogenated Polyisobutene; Ethylhexyl Palmitate; Nylon-12; Paraffin; Hydrogenated Microcrystalline Wax; Polymethyl Methacrylate; Butylene Glycol Cocoate; Mica; Methyl Methacrylate Crosspolymer; Carnauba (Copernica cerifera) Wax; Silica; Hydrogenated Castor Oil; Alumina, Squalene, Calaguala (Polypodium leucotomos) Leaf Extract; Propylene Glycol; Glyceryl Caprylate; Tocopheryl Acetate; Castor (Ricinus communis) Seed Oil; Water; Simethicone; Tocopherol; Beta-Sitosterol; Soybean (Glycine soja) Oil; Paraffinum Liquidum; Fragrance, Linalool, Iron Oxides* (Ferric Oxide Red (CI 77491), Ferric Oxide Yellow (CI 77492), Ferrosoferric Oxide (CI 77499)); Titanium Dioxide* (CI 77891), Bismuth Oxychloride* (CI 77163). * Contains one or more of these ingredients.

NDC 82141-2349-1

Hydrogenated Polyisobutene; Ethylhexyl Palmitate; Nylon-12; Paraffin; Hydrogenated Microcrystalline Wax; Mica; Polymethyl Methacrylate; Butylene Glycol Cocoate; Methyl Methacrylate Crosspolymer; Carnauba (Copernica cerifera) Wax; Silica;
Hydrogenated Castor Oil; Alumina, Squalene, Calaguala (Polypodium leucotomos) Leaf Extract; Propylene Glycol; Glyceryl Caprylate; Tocopheryl Acetate; Castor (Ricinus communis) Seed Oil; Water; Simethicone; Tocopherol; Beta-Sitosterol; Soybean (Glycine soja) Oil; Triethoxycaprylylsilane; Paraffinum Liquidum; Fragrance, Linalool, Iron Oxides* (Ferric Oxide Red (CI 77491), Ferric Oxide Yellow (CI 77492), Ferrosoferric Oxide (CI 77499)); Titanium Dioxide* (CI 77891), Bismuth Oxychloride* (CI 77163). * Contains one or more of these ingredients.

NDC 82141-2351-1

Hydrogenated Polyisobutene; Ethylhexyl Palmitate; Nylon-12; Paraffin; Mica; Polymethyl Methacrylate; Hydrogenated Microcrystalline Wax; Butylene Glycol Cocoate; Methyl Methacrylate Crosspolymer; Carnauba (Copernica cerifera) Wax; Silica; Hydrogenated Castor Oil; Alumina, Squalene, Calaguala (Polypodium leucotomos) Leaf Extract; Propylene Glycol; Glyceryl Caprylate; Tocopheryl Acetate; Castor (Ricinus communis) Seed Oil; Water; Simethicone; Tocopherol; Beta-Sitosterol; Soybean (Glycine soja) Oil; Paraffinum Liquidum; Fragrance, Linalool, Iron Oxides* (Ferric Oxide Red (CI 77491), Ferric Oxide Yellow (CI 77492), Ferrosoferric Oxide (CI 77499)); Titanium Dioxide* (CI 77891), Bismuth Oxychloride* (CI 77163). * Contains one or more of these ingredients.

NDC 82141-2352-1

Hydrogenated Polyisobutene; Ethylhexyl Palmitate; Nylon-12; Paraffin; Hydrogenated Microcrystalline Wax; Polymethyl Methacrylate; Mica; Butylene Glycol Cocoate; Methyl Methacrylate Crosspolymer; Carnauba (Copernica cerifera) Wax; Silica; Hydrogenated Castor Oil; Alumina, Squalene, Calaguala (Polypodium leucotomos) Leaf Extract; Propylene Glycol; Glyceryl Caprylate; Tocopheryl Acetate; Castor (Ricinus communis) Seed Oil; Water; Simethicone; Tocopherol; Beta-Sitosterol; Soybean (Glycine soja) Oil; Triethoxycaprylylsilane; Paraffinum Liquidum; Fragrance, Linalool, Iron Oxides* (Ferric Oxide Red (CI 77491), Ferric Oxide Yellow (CI 77492), Ferrosoferric Oxide (CI 77499)); Titanium Dioxide* (CI 77891), Bismuth Oxychloride* (CI 77163). * Contains one or more of these ingredients.

NDC 82141-2355-1

Hydrogenated Polyisobutene; Ethylhexyl Palmitate; Nylon-12; Paraffin; Hydrogenated Microcrystalline Wax; Butylene Glycol Cocoate; Mica; Polymethyl Methacrylate; Carnauba (Copernica cerifera) Wax; Methyl Methacrylate Crosspolymer; Silica; Hydrogenated Castor Oil; Alumina, Squalene, Calaguala (Polypodium leucotomos) Leaf Extract; Propylene Glycol; Glyceryl Caprylate; Tocopheryl Acetate; Castor (Ricinus communis) Seed Oil; Water; Simethicone; Tocopherol; Beta-Sitosterol; Soybean (Glycine soja) Oil; Triethoxycaprylylsilane; Paraffinum Liquidum; Fragrance, Linalool, Iron Oxides* (Ferric Oxide Red (CI 77491), Ferric Oxide Yellow (CI 77492), Ferrosoferric Oxide (CI 77499)); Titanium Dioxide* (CI 77891), Bismuth Oxychloride* (CI 77163). * Contains one or more of these ingredients.

NDC 82141-0913-1

Hydrogenated Polyisobutene; Ethylhexyl Palmitate; Nylon-12; Paraffin; Hydrogenated Microcrystalline Wax; Butylene Glycol Cocoate; Carnauba (Copernica cerifera) Wax; Mica; Polymethyl Methacrylate; Hydrogenated Castor Oil; Silica; ; Alumina, Squalene, Calaguala (Polypodium leucotomos) Leaf Extract; Propylene Glycol; Glyceryl Caprylate; Tocopheryl Acetate; Castor (Ricinus communis) Seed Oil; Water; Simethicone; Tocopherol; Beta-Sitosterol; Soybean (Glycine soja) Oil; Sodium Stearate; Cethearyl Alcohol; Ceteareth-20; Calcium Chloride; Triethoxycaprylylsilane; Fragrance, Linalool, Iron Oxides* (Ferric Oxide Red (CI 77491), Ferric Oxide Yellow (CI 77492), Ferrosoferric Oxide (CI 77499)); Bismuth Oxychloride* (CI 77163). * Contains one or more of these ingredients.

toty Ilumina CC Creamy Compact 1C

NDC 82141-2344-1 (toty Ilumina CC Creamy Compact 1C)

toty.®
ILUMINA
CC CREAMY COMPACT
SPF 50+
SKIN-PERFECTING BLURRING BALM

BALSAMO PERFECCIONADOR DIFUMINADOR
.....................................................................................

BROAD SPECTRUM SPF 50+ MINERAL SUNSCREEN
WATER RESISTANT (80 MINUTES)

PROTECCION SOLAR MINERAL AMPLIO ESPECTRO SPF 50+
RESISTENTE AL AGUA (80 MINUTOS)

0.35 oz/10g

toty Ilumina CC Creamy Compact 2N

NDC 82141-2345-1 (toty Ilumina CC Creamy Compact 2N)

toty.®
ILUMINA
CC CREAMY COMPACT
SPF 50+
SKIN-PERFECTING BLURRING BALM

BALSAMO PERFECCIONADOR DIFUMINADOR
.....................................................................................

BROAD SPECTRUM SPF 50+ MINERAL SUNSCREEN
WATER RESISTANT (80 MINUTES)

PROTECCION SOLAR MINERAL AMPLIO ESPECTRO SPF 50+
RESISTENTE AL AGUA (80 MINUTOS)

0.35 oz/10g

toty Ilumina CC Creamy Compact 2W

NDC 82141-2346-1 (toty Ilumina CC Creamy Compact 2W)

toty.®
ILUMINA
CC CREAMY COMPACT
SPF 50+
SKIN-PERFECTING BLURRING BALM

BALSAMO PERFECCIONADOR DIFUMINADOR
.....................................................................................

BROAD SPECTRUM SPF 50+ MINERAL SUNSCREEN
WATER RESISTANT (80 MINUTES)

PROTECCION SOLAR MINERAL AMPLIO ESPECTRO SPF 50+
RESISTENTE AL AGUA (80 MINUTOS)

0.35 oz/10g

toty Ilumina CC Creamy Compact 2C

NDC 82141-2347-1 (toty Ilumina CC Creamy Compact 2C)

toty.®
ILUMINA
CC CREAMY COMPACT
SPF 50+
SKIN-PERFECTING BLURRING BALM

BALSAMO PERFECCIONADOR DIFUMINADOR
.....................................................................................

BROAD SPECTRUM SPF 50+ MINERAL SUNSCREEN
WATER RESISTANT (80 MINUTES)

PROTECCION SOLAR MINERAL AMPLIO ESPECTRO SPF 50+
RESISTENTE AL AGUA (80 MINUTOS)

0.35 oz/10g

toty Ilumina CC Creamy Compact 3N

NDC 82141-2348-1 (toty Ilumina CC Creamy Compact 3N)

toty.®
ILUMINA
CC CREAMY COMPACT
SPF 50+
SKIN-PERFECTING BLURRING BALM

BALSAMO PERFECCIONADOR DIFUMINADOR
.....................................................................................

BROAD SPECTRUM SPF 50+ MINERAL SUNSCREEN
WATER RESISTANT (80 MINUTES)

PROTECCION SOLAR MINERAL AMPLIO ESPECTRO SPF 50+
RESISTENTE AL AGUA (80 MINUTOS)

0.35 oz/10g

toty Ilumina CC Creamy Compact 3W

NDC 82141-2349-1 (toty Ilumina CC Creamy Compact 3W)

toty.®
ILUMINA
CC CREAMY COMPACT
SPF 50+
SKIN-PERFECTING BLURRING BALM

BALSAMO PERFECCIONADOR DIFUMINADOR
.....................................................................................

BROAD SPECTRUM SPF 50+ MINERAL SUNSCREEN
WATER RESISTANT (80 MINUTES)

PROTECCION SOLAR MINERAL AMPLIO ESPECTRO SPF 50+
RESISTENTE AL AGUA (80 MINUTOS)

0.35 oz/10g

toty Ilumina CC Creamy Compact 3C

NDC 82141-2350-1 (toty Ilumina CC Creamy Compact 3C)

toty.®
ILUMINA
CC CREAMY COMPACT
SPF 50+
SKIN-PERFECTING BLURRING BALM

BALSAMO PERFECCIONADOR DIFUMINADOR
.....................................................................................

BROAD SPECTRUM SPF 50+ MINERAL SUNSCREEN
WATER RESISTANT (80 MINUTES)

PROTECCION SOLAR MINERAL AMPLIO ESPECTRO SPF 50+
RESISTENTE AL AGUA (80 MINUTOS)

0.35 oz/10g

toty Ilumina CC Creamy Compact 4N

NDC 82141-2351-1 (toty Ilumina CC Creamy Compact 4N)

toty.®
ILUMINA
CC CREAMY COMPACT
SPF 50+
SKIN-PERFECTING BLURRING BALM

BALSAMO PERFECCIONADOR DIFUMINADOR
.....................................................................................

BROAD SPECTRUM SPF 50+ MINERAL SUNSCREEN
WATER RESISTANT (80 MINUTES)

PROTECCION SOLAR MINERAL AMPLIO ESPECTRO SPF 50+
RESISTENTE AL AGUA (80 MINUTOS)

0.35 oz/10g

toty Ilumina CC Creamy Compact 4W

NDC 82141-2352-1 (toty Ilumina CC Creamy Compact 4W)

toty.®
ILUMINA
CC CREAMY COMPACT
SPF 50+
SKIN-PERFECTING BLURRING BALM

BALSAMO PERFECCIONADOR DIFUMINADOR
.....................................................................................

BROAD SPECTRUM SPF 50+ MINERAL SUNSCREEN
WATER RESISTANT (80 MINUTES)

PROTECCION SOLAR MINERAL AMPLIO ESPECTRO SPF 50+
RESISTENTE AL AGUA (80 MINUTOS)

0.35 oz/10g

toty Ilumina CC Creamy Compact 5W1

NDC 82141-2355-1 (toty Ilumina CC Creamy Compact 5W1)

toty.®
ILUMINA
CC CREAMY COMPACT
SPF 50+
SKIN-PERFECTING BLURRING BALM

BALSAMO PERFECCIONADOR DIFUMINADOR
.....................................................................................

BROAD SPECTRUM SPF 50+ MINERAL SUNSCREEN
WATER RESISTANT (80 MINUTES)

PROTECCION SOLAR MINERAL AMPLIO ESPECTRO SPF 50+
RESISTENTE AL AGUA (80 MINUTOS)

0.35 oz/10g

toty Ilumina CC Creamy Compact 6N

NDC 82141-0913-1 (toty Ilumina CC Creamy Compact 6N)

toty.®
ILUMINA
CC CREAMY COMPACT
SPF 50+
SKIN-PERFECTING BLURRING BALM

BALSAMO PERFECCIONADOR DIFUMINADOR
.....................................................................................

BROAD SPECTRUM SPF 50+ MINERAL SUNSCREEN
WATER RESISTANT (80 MINUTES)

PROTECCION SOLAR MINERAL AMPLIO ESPECTRO SPF 50+
RESISTENTE AL AGUA (80 MINUTOS)

0.35 oz/10g